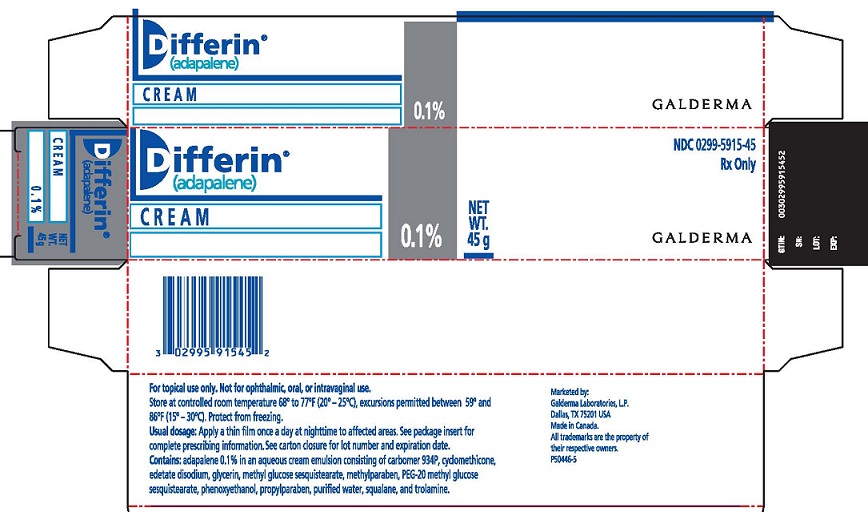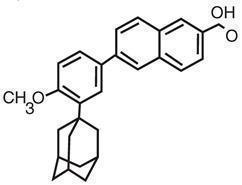 DRUG LABEL: Differin
NDC: 0299-5915 | Form: CREAM
Manufacturer: GALDERMA LABORATORIES, L.P
Category: prescription | Type: HUMAN PRESCRIPTION DRUG LABEL
Date: 20221020

ACTIVE INGREDIENTS: ADAPALENE 1 mg/1 g
INACTIVE INGREDIENTS: CARBOMER HOMOPOLYMER TYPE B (ALLYL PENTAERYTHRITOL OR ALLYL SUCROSE CROSSLINKED); CYCLOMETHICONE; EDETATE DISODIUM; METHYL GLUCOSE SESQUISTEARATE; GLYCERIN; METHYLPARABEN; PEG-20 METHYL GLUCOSE SESQUISTEARATE; PHENOXYETHANOL; PROPYLPARABEN; WATER; SQUALANE; TROLAMINE

Differin (adapalene) Cream, 0.1%
Rx Only
For topical use only. Not for ophthalmic, oral, or intravaginal use.

DESCRIPTION

DIFFERIN® (adapalene) Cream, 0.1%, contains adapalene 0.1% in an aqueous cream emulsion consisting of carbomer 934P, cyclomethicone, edetate disodium, glycerin, methyl glucose sesquistearate, methylparaben, PEG-20 methyl glucose sesquistearate, phenoxyethanol, propylparaben, purified water, squalane, and trolamine.

The chemical name of adapalene is 6-[3-(1-adamantyl)-4-methoxyphenyl]-2-naphthoic acid. It is a white to off-white powder which is soluble in tetrahydrofuran, sparingly soluble in ethanol, and practically insoluble in water. The molecular formula is C28H28O3 and molecular weight is 412.53. Adapalene is represented by the following structural formula.

CLINICAL PHARMACOLOGY:

Mechanism of Action:

Adapalene acts on retinoid receptors. Biochemical and pharmacological profile studies have demonstrated that adapalene is a modulator of cellular differentiation, keratinization, and inflammatory processes all of which represent important features in the pathology of acne vulgaris.

Mechanistically, adapalene binds to specific retinoic acid nuclear receptors but does not bind to the cytosolic receptor protein. Although the exact mode of action of adapalene is unknown, it is suggested that topical adapalene normalizes the differentiation of follicular epithelial cells resulting in decreased microcomedone formation.

Pharmacokinetics:

Absorption of adapalene from DIFFERIN® Cream through human skin is low. In a pharmacokinetic study with six acne patients treated once daily for 5 days with 2 grams of DIFFERIN® Cream applied to 1000 cm^2 of acne involved skin, there were no quantifiable amounts (limit of quantification = 0.35 ng/mL) of adapalene in the plasma samples from any patient. Excretion appears to be primarily by the biliary route.

INDICATIONS AND USAGE:

DIFFERIN® Cream is indicated for the topical treatment of acne vulgaris.

CLINICAL STUDIES:

Two vehicle-controlled clinical studies were conducted in patients 12 to 30 years of age with mild to moderate acne vulgaris, in which DIFFERIN® Cream was compared with its vehicle. Patients were instructed to apply their treatment medication once daily at bedtime for 12 weeks. In one study patients were provided with a soapless cleanser and were encouraged to refrain from using moisturizers. No other topical medications, other than DIFFERIN® Cream, were to be applied to the face during the studies. DIFFERIN® Cream was significantly more effective than its vehicle in the reduction of acne lesion counts. The mean percent reduction in lesion counts from baseline after treatment for 12 weeks are presented in the following table:

MEAN PERCENT REDUCTION IN LESION COUNTS FROM BASELINE TO WEEK 12
Efficacy Variable | Study No. 1 |  | Study No. 2
Efficacy Variable | Adapalene Cream, 0.1% N=119 | Cream Vehicle N=118 | Adapalene Cream, 0.1% N=175 | Cream Vehicle N=175
Non-inflammatory lesions | 34% | 18% | 35% | 15%
Inflammatory lesions | 32% | 17% | 14% | 6%
Total lesions | 34% | 18% | 30% | 15%

The trend in the Investigator’s global assessment of severity supported the efficacy of DIFFERIN® Cream when compared to the cream vehicle.

CONTRAINDICATIONS:

DIFFERIN® Cream should not be administered to individuals who are hypersensitive to adapalene or any of the components in the cream vehicle.

PRECAUTIONS:

General:

Certain cutaneous signs and symptoms of treatment such as erythema, dryness, scaling, burning, or pruritus may be experienced with use of DIFFERIN® Cream. These are most likely to occur during the first two to four weeks of treatment, are mostly mild to moderate in intensity, and usually lessen with continued use of the medication. Depending upon the severity of these side effects, patients should be instructed to reduce the frequency of application or discontinue use.

If a reaction suggesting sensitivity or chemical irritation occurs, use of the medication should be discontinued. Exposure to sunlight, including sunlamps, should be minimized during use of adapalene. Patients who normally experience high levels of sun exposure, and those with inherent sensitivity to sun, should be warned to exercise caution. Use of sunscreen products and protective clothing over treated areas is recommended when exposure cannot be avoided. Weather extremes, such as wind or cold, also may be irritating to patients under treatment with adapalene.

Avoid contact with the eyes, lips, angles of the nose, and mucous membranes. The product should not be applied to cuts, abrasions, eczematous or sunburned skin. As with other retinoids, use of “waxing” as a depilatory method should be avoided on skin treated with adapalene.

Information for Patients:

Patients using DIFFERIN® Cream should receive the following information and instructions:

1. This medication is to be used only as directed by the physician.
2. It is for external use only.
3. Avoid contact with the eyes, lips, angles of the nose, and mucous membranes.
4. Cleanse area with a mild or soapless cleanser before applying this medication.
5. Moisturizers may be used if necessary; however, products containing alpha hydroxy or glycolic acids should be avoided.
6. Exposure of the eye to this medication may result in reactions such as swelling, conjunctivitis, and eye irritation.
7. This medication should not be applied to cuts, abrasions, eczematous or sunburned skin.
8. Wax epilation should not be performed on treated skin due to the potential for skin erosions.
9. During the early weeks of therapy, an apparent exacerbation of acne may occur. This is due to the action of this medication on previously unseen lesions and should not be considered a reason to discontinue therapy. Overall clinical benefit may be noticed after two weeks of therapy, but at least eight weeks are required to obtain consistent beneficial effects.

Drug Interactions:

As DIFFERIN® Cream has the potential to produce local irritation in some patients, concomitant use of other potentially irritating topical products (medicated or abrasive soaps and cleansers, soaps and cosmetics that have a strong drying effect, and products with high concentrations of alcohol, astringents, spices or lime rind) should be approached with caution. Particular caution should be exercised in using preparations containing sulfur, resorcinol, or salicylic acid in combination with DIFFERIN® Cream. If these preparations have been used, it is advisable not to start therapy with DIFFERIN® Cream until the effects of such preparations in the skin have subsided.

Carcinogenesis, Mutagenesis, Impairment of Fertility:

Carcinogenicity studies with adapalene have been conducted in mice at topical doses of 0.4, 1.3, and 4.0 mg/kg/day, and in rats at oral doses of 0.15, 0.5, and 1.5 mg/kg/day. These doses are up to 8 times (mice) and 6 times (rats) in terms of mg/m^2/day the maximum potential exposure at the recommended topical human dose (MRHD), assumed to be 2.5 grams DIFFERIN® Cream, which is approximately 1.5 mg/m^2 adapalene. In the oral study, increased incidence of benign and malignant pheochromocytomas in the adrenal medullas of male rats was observed.

No photocarcinogenicity studies were conducted. Animal studies have shown an increased risk of skin neoplasms with the use of pharmacologically similar drugs (e.g., retinoids) when exposed to UV irradiation in the laboratory or to sunlight. Although the significance of these studies to human use is not clear, patients should be advised to avoid or minimize exposure to either sunlight or artificial UV irradiation sources.

Adapalene did not exhibit mutagenic or genotoxic effects in vivo (mouse micronucleous test) and in vitro (Ames test, Chinese hamster ovary cell assay, mouse lymphoma TK assay) studies.

Reproductive function and fertility studies were conducted in rats administered oral doses of adapalene in amounts up to 20 mg/kg/day (up to 80 times the MRHD based on mg/m^2 comparisons). No effects of adapalene were found on the reproductive performance or fertility of the FO males or females. There were also no detectable effects on the growth, development and subsequent reproductive function of the F1 generation.

Pregnancy:

Teratogenic effects. Pregnancy Category C. No teratogenic effects were seen in rats at oral doses of 0.15 to 5.0 mg/kg/day adapalene (up to 20 times the MRHD based on mg/m^2 comparisons). However, adapalene administered orally at doses of ≥ 25 mg/kg, (100 times the MRHD for rats or 200 times MRHD for rabbits) has been shown to be teratogenic. Cutaneous teratology studies in rats and rabbits at doses of 0.6, 2.0, and 6.0 mg/kg/day (24 times the MRHD for rats or 48 times the MRHD for rabbits) exhibited no fetotoxicity and only minimal increases in supernumerary ribs in rats. There are no adequate and well-controlled studies in pregnant women. Adapalene should be used during pregnancy only if the potential benefit justifies the potential risk to the fetus.

Nursing Mothers:

It is not known whether this drug is excreted in human milk. Because many drugs are excreted in human milk, caution should be exercised when DIFFERIN® Cream is administered to a nursing woman.

Pediatric Use:

Safety and effectiveness in pediatric patients below the age of 12 have not been established.

Geriatric Use:

Clinical studies of DIFFERIN® Cream were conducted in patients 12 to 30 years of age with acne vulgaris and therefore did not include subjects 65 years and older to determine whether they respond differently than younger subjects. Other reported clinical experience has not identified differences in responses between the elderly and younger patients.

ADVERSE REACTIONS:

In controlled clinical trials, local cutaneous irritation was monitored in 285 acne patients who used DIFFERIN® Cream once daily for 12 weeks. The frequency and severity of erythema, scaling, dryness, pruritus and burning were assessed during these studies. The incidence of local cutaneous irritation with DIFFERIN® Cream from the controlled clinical studies is provided in the following table:

Incidence of Local Cutaneous Irritation with DIFFERIN® Cream from Controlled Clinical Studies (N=285)
 | None | Mild | Moderate | Severe
Erythema | 52% (148) | 38% (108) | 10% (28) | < 1% (1)
Scaling | 58% (166) | 35% (100) | 6% (18) | <1% (1)
Dryness | 48% (136) | 42% (121) | 9% (26) | <1% (2)
Pruritus (persistent) | 74% (211) | 21% (61) | 4% (12) | <1% (1)
Burning/Stinging (persistent) | 71% (202) | 24% (69) | 4% (12) | <1% (2)

Other reported local cutaneous adverse events in patients who used DIFFERIN® Cream once daily included: sunburn (2%), skin discomfort-burning and stinging (1%) and skin irritation (1%). Events occurring in less than 1% of patients treated with DIFFERIN® Cream included: acne flare, dermatitis and contact dermatitis, eyelid edema, conjunctivitis, erythema, pruritus, skin discoloration, rash, and eczema.

OVERDOSAGE:

DIFFERIN® Cream is intended for cutaneous use only. If the medication is applied excessively, no more rapid or better results will be obtained and marked redness, scaling, or skin discomfort may occur. The acute oral toxicity of DIFFERIN® Cream in mice and rats is greater than 10 mL/kg. Chronic ingestion of the drug may lead to the same side effects as those associated with excessive oral intake of Vitamin A.

DOSAGE AND ADMINISTRATION:

DIFFERIN® Cream should be applied to affected areas of the skin, once daily at nighttime. A thin film of the cream should be applied to the skin areas where acne lesions appear, using enough to cover the entire affected areas lightly. A mild transitory sensation of warmth or slight stinging may occur shortly after the application of DIFFERIN® Cream.

HOW SUPPLIED:

DIFFERIN® (adapalene) Cream, 0.1% is supplied in the following size:

45 g tube – NDC 0299-5915-45

Storage: Store at controlled room temperature 68° to 77°F (20°-25°C), with excursions permitted between 59° and 86°F (15°-30°C). Protect from freezing.

Marketed by:

GALDERMA LABORATORIES, L.P. Dallas, Texas 75201 USA

Manufactured by:

G Production Inc., Baie d'Urfé, QC, H9X 3S4 Canada

Made in Canada.
All trademarks are the property of their respective owners.

P50448-2

Revised: October 2022

Package

Differin®

(adapalene)

CREAM

0.1%
NET WT. 45 g

NDC 0299-5915-45
Rx Only

GALDERMA

For topical use only. Not for opthalmic, oral, or intravaginal use.

Store at controlled room temperature 68° to 77°F (20°-25°C), excursions permitted between 59° and 86°F (15°-30°C). Protect from freezing.

Usual dosage: Apply a thin film once a day at nighttime to affected areas. See package insert for complete prescribing information. See carton closure for lot number and expiration date.

Contains: adapalene 0.1% in an aqueous cream emulsion consisting of carbomer 934P, cyclomethicone, edetate disodium, glycerin, methyl glucose sesquistearate, methylparaben, PEG-20 methyl glucose sesquistearate, phenoxyethanol, propylparaben, purified water, squalane, and trolamine.

Marketed by:

GALDERMA LABORATORIES, L.P.

Dallas, Texas 75201 USA
Made in Canada

All trademarks are the property of their respective owners.

P50446-5